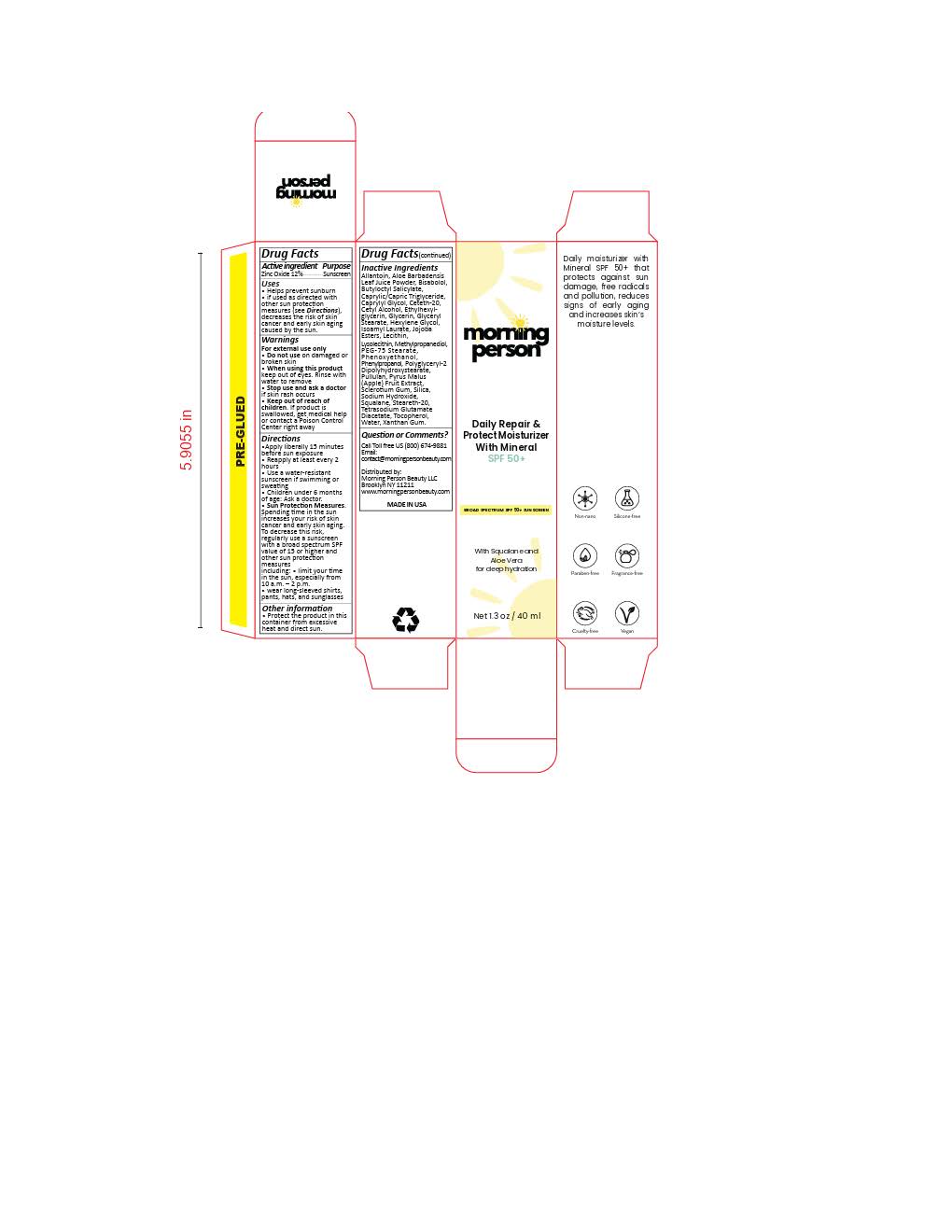 DRUG LABEL: Morning Person Daily Repair Protect Moisturizer
NDC: 84846-1039 | Form: LOTION
Manufacturer: Morning Person Beauty
Category: otc | Type: HUMAN OTC DRUG LABEL
Date: 20251117

ACTIVE INGREDIENTS: ZINC OXIDE 132 mg/1 mL
INACTIVE INGREDIENTS: BUTYLOCTYL SALICYLATE; CETETH-20; PULLULAN; SQUALANE; STEARETH-20; CYCLODEXTRINS; LECITHIN, SOYBEAN; POLYGLYCERYL-2 DIPOLYHYDROXYSTEARATE; HYDROLYZED JOJOBA ESTERS (ACID FORM); METHYLPROPANEDIOL; CAPRYLYL GLYCOL; PHENYLPROPANOL; XANTHAN GUM; ISOAMYL LAURATE; HEXYLENE GLYCOL; TOCOPHEROL; CETYL ALCOHOL; ETHYLHEXYLGLYCERIN; GLYCERIN; SILICON DIOXIDE; WATER; .ALPHA.-BISABOLOL, (+)-

Morning Person Daily Repair Protect Moisturizer